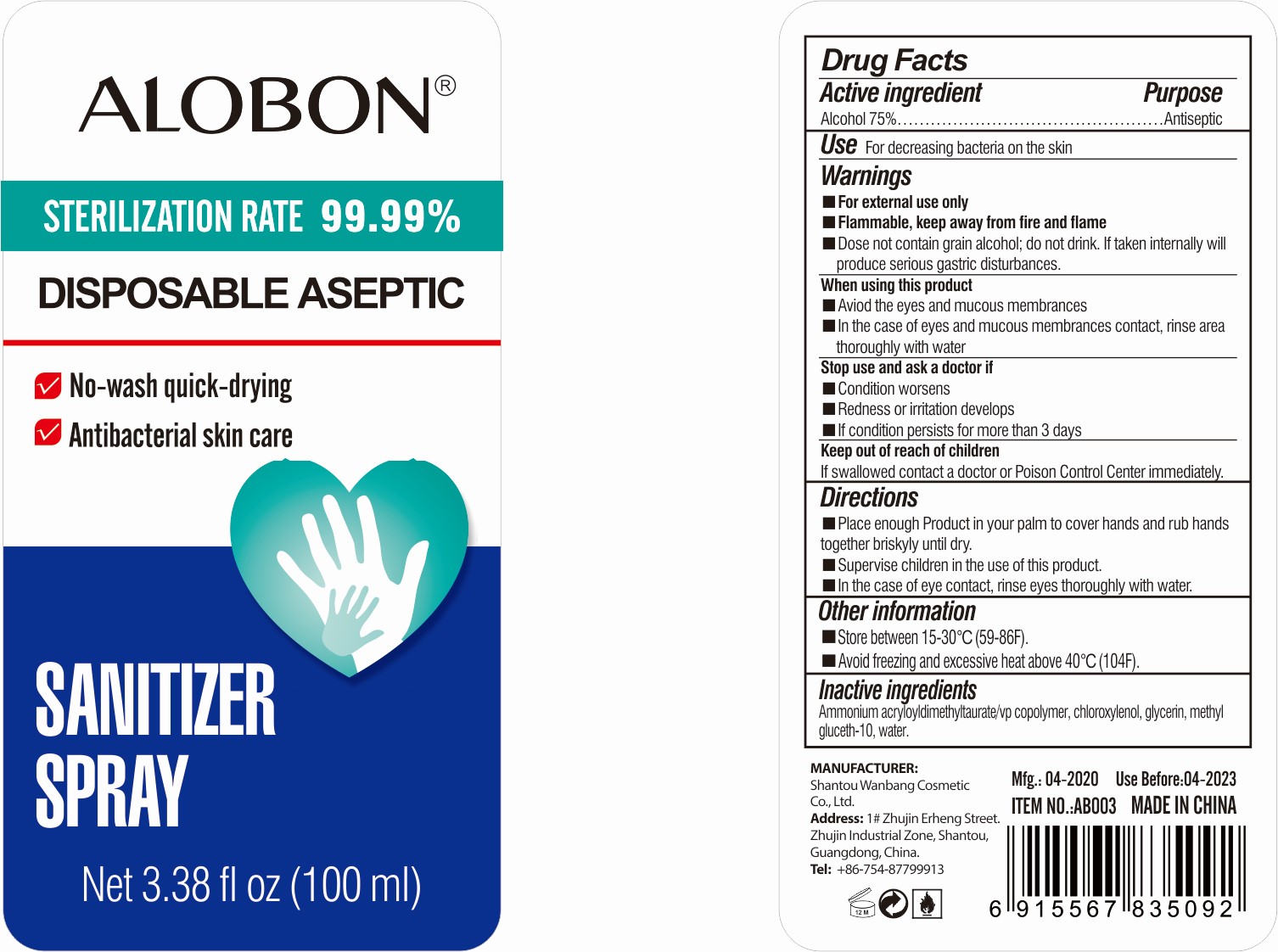 DRUG LABEL: ALOBON SanitizerSpray
NDC: 78692-613 | Form: SPRAY
Manufacturer: Shantou Wanbang Cosmetic Co., Ltd.
Category: otc | Type: HUMAN OTC DRUG LABEL
Date: 20200818

ACTIVE INGREDIENTS: ALCOHOL 75 mL/100 mL
INACTIVE INGREDIENTS: GLYCERIN; WATER; METHYL GLUCETH-10; CARBOMER INTERPOLYMER TYPE A (55000 CPS); CHLOROXYLENOL

Active Ingredient

Alcohol 75%

Purpose

Antiseptic

Use

For decreasing bacteria on the skin

Warnings

- For external use only
- Flammable, keep away from fire and flame
- Dose not contain grain alcohol; do not drink. If taken internally will produce serious gastric disturbances.

When using this product

- Aviod the eyes and mucous membrances
- In the case of eyes and mucous membrances contact, rinse area thoroughly with water

Stop use and ask a doctor if

- Condition worsens
- Redness or irritation develops
- If condition persists for more than 3 days

Keep out of reach of children

If swallowed contact a doctor or Poison Control Center immediately.

Directions

- Place enough Product in your palm to cover hands and rub hands together briskyly until dry.
- Supervise children in the use of this product.
- In the case of eye contact, rinse eyes thoroughly with water.

Other information

- Store between 15-30°C (59-86F).
- Avoid freezing and excessive heat above 40°C (104F).

Inactive ingredients

Ammonium acryloyldimethyltaurate/vp copolymer, chloroxylenol, glycerin, methyl gluceth-10, water.

Package Label/Principal Display Panel

NDC 78692-613-34; 100 mL